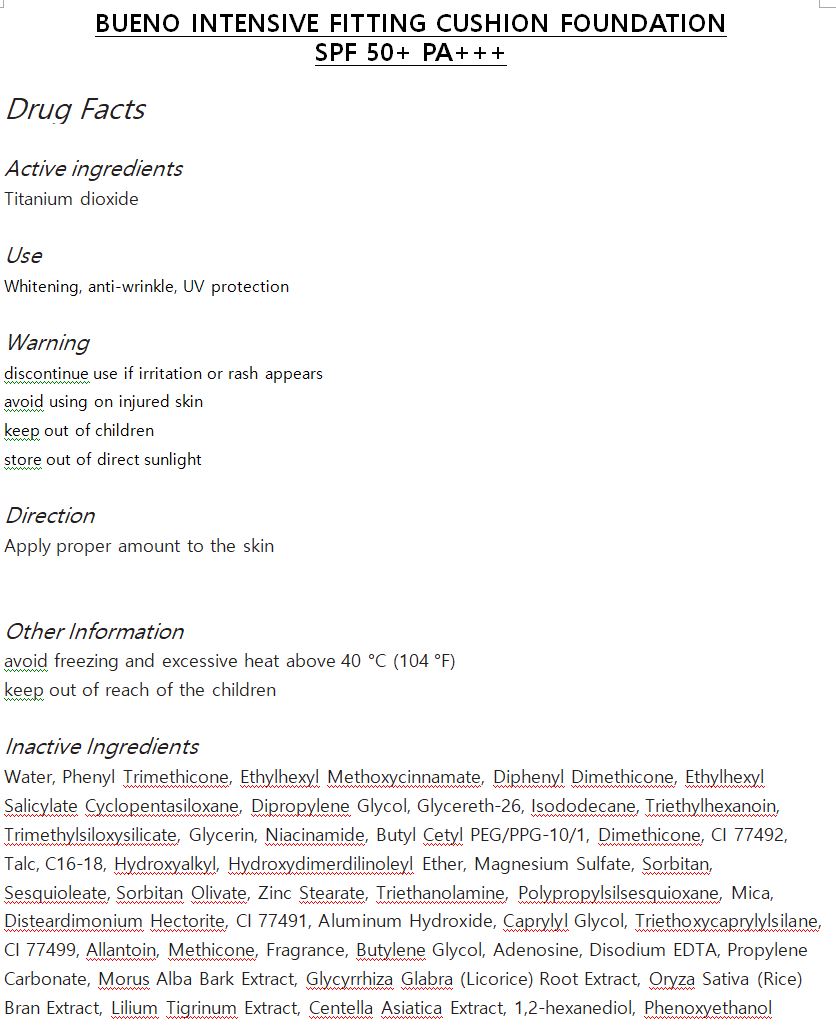 DRUG LABEL: BUENO INTENSIVE FITTING CUSHION FOUNDATION SPF 50 PA
NDC: 73261-0004 | Form: POWDER
Manufacturer: Bueno MEDITECH
Category: otc | Type: HUMAN OTC DRUG LABEL
Date: 20190803

ACTIVE INGREDIENTS: TITANIUM DIOXIDE 11.4072 g/100 g
INACTIVE INGREDIENTS: BUTYLENE GLYCOL

Drug Facts

ACTIVE INGREDIENT

titanium dioxide

INACTIVE INGREDIENT

Water
Phenyl Trimethicone
Ethylhexyl Methoxycinnamate
Diphenyl Dimethicone
Ethylhexyl Salicylate
Cyclopentasiloxane
Dipropylene Glycol
Glycereth-26
Isododecane
Triethylhexanoin
Trimethylsiloxysilicate
Glycerin
Niacinamide
Butyl
Cetyl PEG/PPG-10/1
Dimethicone
CI 77492
Talc
C16-18 Hydroxyalkyl
Hydroxydimerdilinoleyl Ether
Magnesium Sulfate
Sorbitan Sesquioleate
Sorbitan Olivate
Zinc Stearate
Triethanolamine
Polypropylsilsesquioxane
Dimethicone/Vinyl
Dimethicone Crosspolymer
Mica
Disteardimonium Hectorite
CI 77491
Aluminum Hydroxide
Caprylyl Glycol
Triethoxycaprylylsilane
CI 77499
Allantoin
Methicone
Fragrance
Butylene Glycol
Adenosine
Disodium EDTA
Propylene Carbonate
Morus Alba Bark Extract
Glycyrrhiza Glabra (Licorice)
Root Extract
Oryza Sativa (Rice) Bran Extract
Lilium Tigrinum Extract
Centella Asiatica Extract
1,2-hexanediol
Phenoxyethanol

PURPOSE

Whitening, anti-wrinkle, UV protection

keep out of reach of the children

INDICATIONS AND USAGE

apply proper amount to the skin

WARNINGS

discontinue use if irritation or rash appears

avoid using on injured skin

keep out of childres

store out of direct sunlight

DOSAGE AND ADMINISTRATION

for topical use only